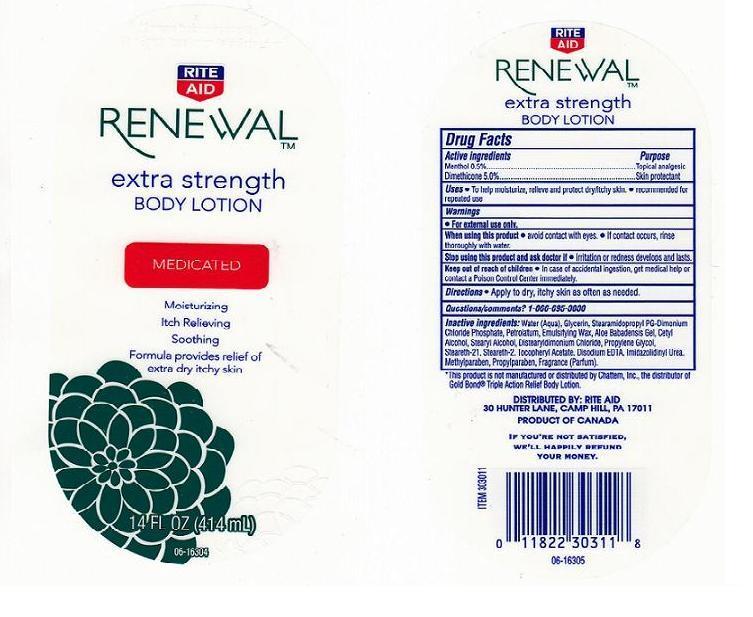 DRUG LABEL: RENEWAL
NDC: 11822-3351 | Form: LOTION
Manufacturer: RITE AID 
Category: otc | Type: HUMAN OTC DRUG LABEL
Date: 20100714

ACTIVE INGREDIENTS: MENTHOL 0.5 mL/100 mL; DIMETHICONE 5.0 mL/100 mL

DRUG FACTS BOX(BACK LABEL)

ACTIVE INGREDIENTS

- MENTHOL 0.5% (TOPICAL ANALGESIC)
- DIMETHICONE 5.0% (SKIN PROTECTANT)

USES AND DIRECTIONS

- USES: TO HELP MOISTURIZE, RELIEVE AND PROTECT DRY/ITCHY SKIN. RECOMMENDED FOR REPEATED USE.
- DIRECTIONS: APPLY TO DRY, ITCHY SKIN AS OFTEN AS NEEDED

WARNINGS

- FOR EXTERNAL USE ONLY.

WHEN USING THIS PRODUCT

- AVOID CONTACT WITH EYES. IF CONTACT OCCURS, RINSE THOROUGHLY WITH WATER.

STOP USING THIS PRODUCT AND ASK A DOCTOR IF

- IRRITATION OR REDNESS DEVELOPS AND LASTS.

KEEP OUT OF REACH OF CHILDREN

- IN CASE OF ACCIDENTAL INGESTION, GET MEDICAL HELP OR CONTACT A POISON CONTROL CENTER IMMEDIATELY.

QUESTIONS/COMMENTS?

1-866-695-3030

PACKAGE FRONT AND BACK LABELS (14OZ)

- 14OZ FRONT AND BACK LABELS: ra14.jpg